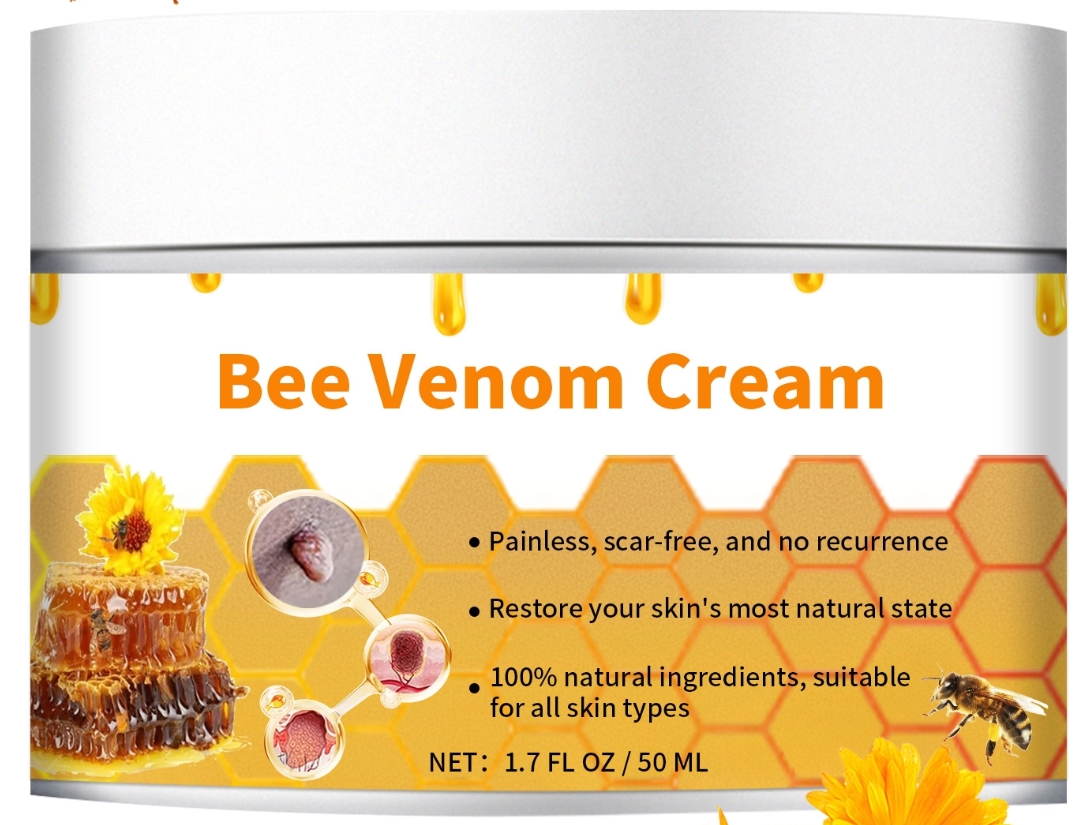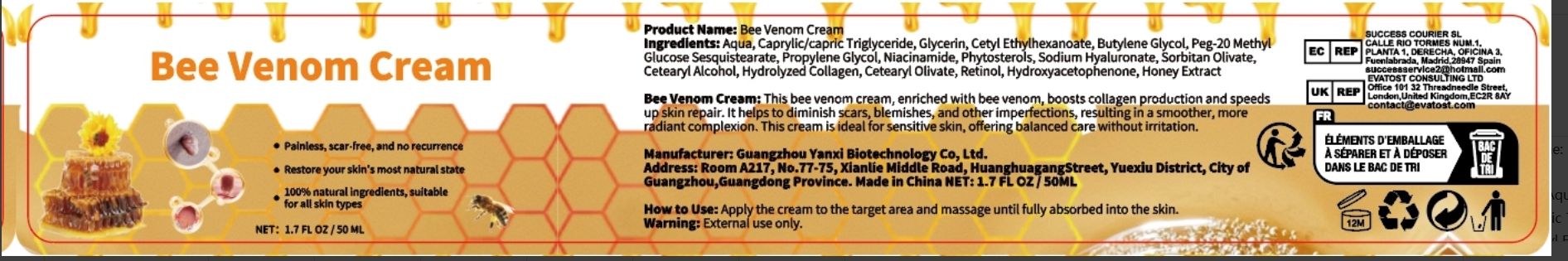 DRUG LABEL: Bee Venom Cream
NDC: 84025-191 | Form: CREAM
Manufacturer: Guangzhou Yanxi Biotechnology Co.. Ltd
Category: otc | Type: HUMAN OTC DRUG LABEL
Date: 20240923

ACTIVE INGREDIENTS: GLYCERIN 5 mg/50 mL; CETYL ETHYLHEXANOATE 3 mg/50 mL
INACTIVE INGREDIENTS: WATER

DOSAGE AND ADMINISTRATION

Cream for moisturizing the skin and repairing skin damage

WARNINGS

Keep out of children

INDICATIONS AND USAGE

For daily skin care

keep out of children

INACTIVE INGREDIENT

AQUA

PURPOSE

Effectively smoothes and moisturizes the skin